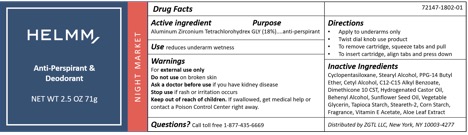 DRUG LABEL: Helmm Antiperspirant Deodorant Night Market
NDC: 72147-1802 | Form: GEL
Manufacturer: ZGTL, LLC
Category: otc | Type: HUMAN OTC DRUG LABEL
Date: 20260204

ACTIVE INGREDIENTS: ALUMINUM ZIRCONIUM TETRACHLOROHYDREX GLY 18 g/57 g
INACTIVE INGREDIENTS: STARCH, CORN; PPG-14 BUTYL ETHER; STARCH, TAPIOCA; STEARETH-2; CYCLOMETHICONE 5; STEARYL ALCOHOL; C12-15 ALKYL ETHYLHEXANOATE; DOCOSANOL; SUNFLOWER OIL; .ALPHA.-TOCOPHEROL ACETATE; ALOE VERA LEAF; CETYL ALCOHOL; DIMETHICONE 20; HYDROGENATED CASTOR OIL

Helmm Antiperspirant and Deodorant - Night Market

ACTIVE INGREDIENT

Aluminum Zirconium Tetrachlorohydren GLY (18%)

INACTIVE INGREDIENT

Cyclopentasiloxane, Stearyl Alcohol, PPG-14 Butyl Ether, Cetyl Alcohol, C12-C15 Alkyl Benzoate, Dimethicone 10 CST, Hydrogenated Castor Oil, Behenyl Alcohol, Sunflower Seed Oil, Vegetable Glycerin, Tapioca Starch, Steareth-2, Corn Starch, Fragrance, Vitamin E Acetate, Aloe Leaf Extract

INDICATIONS AND USAGE

Uses: reduces underarm wetness

Warnings
For external use only
Do not use on broken skin
Ask a doctor before use if you have kidney disease
Stop use if rash or irritation occurs
Keep out of reach of children. If swallowed, get medical help or contact a Poison Control Center right away.

Keep out of reach of children. If swallowed, get medical help or contact a Poison Control Center right away.

DOSAGE AND ADMINISTRATION

- Apply to underarms only
- Twist dial knob use product
- To remove cartridge, squeeze tabs and pull
- To insert cartridge, align tabs and press down

PURPOSE

Uses: reduces underarm wetness